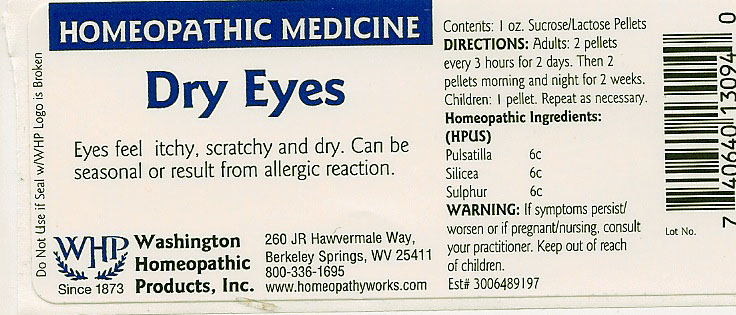 DRUG LABEL: Dry Eyes
NDC: 68428-006 | Form: PELLET
Manufacturer: Washington Homeopathic Products
Category: homeopathic | Type: HUMAN OTC DRUG LABEL
Date: 20101015

ACTIVE INGREDIENTS: PULSATILLA VULGARIS 6 [hp_C]/1 1; SILICON DIOXIDE 6 [hp_C]/1 1; SULFUR 6 [hp_C]/1 1
INACTIVE INGREDIENTS: SUCROSE; LACTOSE

DRUG FACTS

ACTIVE INGREDIENTS

PULSATILLA 6C

SILICEA 6C

SULPHUR 6C

USES

To relieve the symptoms of eyes feel itchy, scratchy and dry. Can be seasonal or result from allergic reaction.

KEEP OUT OF REACH OF CHILDREN

Keep this and all medicines out of reach of children.

INDICATIONS

PULSATILLA weeping

SILICEA Formation of pus

SULPHUR Skin problems

STOP USE AND ASK DOCTOR

If symptoms persist/worsen or if pregnant/nursing, stop use and consult your practitioner.

DIRECTIONS

Adults 2 pellets every 3 hours for 2 days. Then 2 pellets morning and night for 2 weeks.

Children: 1 pellet. Repeat as necessary.

INACTIVE INGREDIENTS

Sucrose/Lactose

PRINCIPAL DISPLAY PANEL

Enter section text here